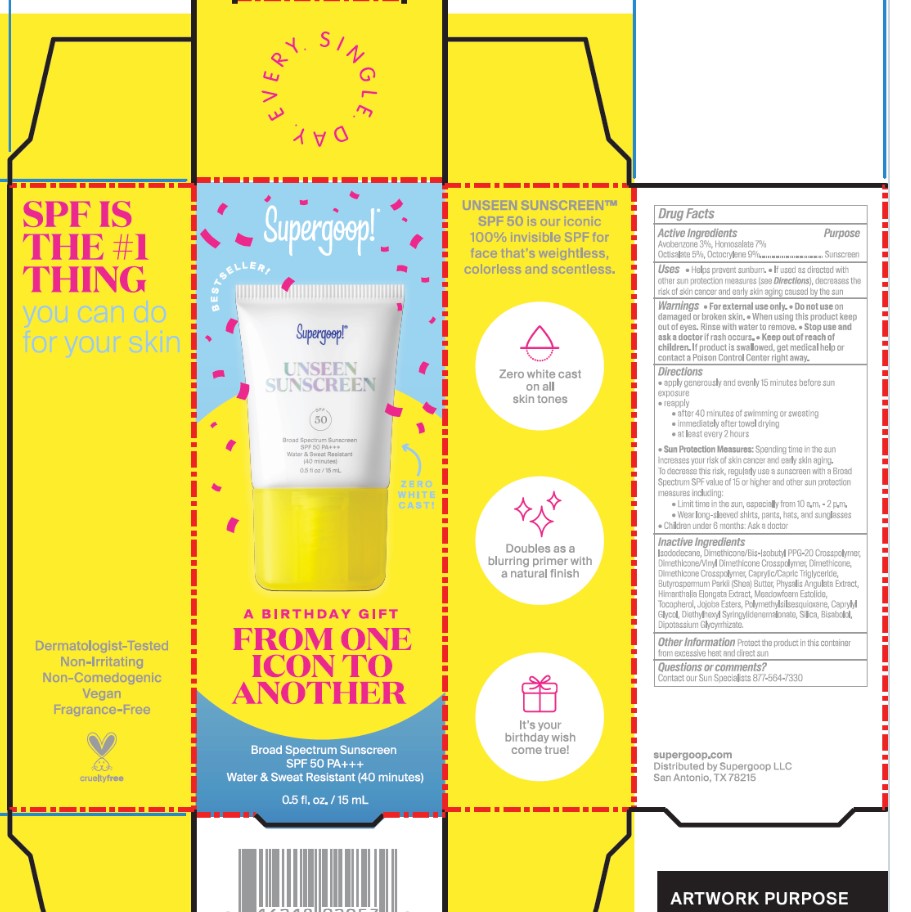 DRUG LABEL: Unseen Sunscreen Broad Spectrum SPF 40
NDC: 75936-164 | Form: CREAM
Manufacturer: Supergoop, LLC
Category: otc | Type: HUMAN OTC DRUG LABEL
Date: 20240807

ACTIVE INGREDIENTS: AVOBENZONE 3 g/100 mL; HOMOSALATE 8 g/100 mL; OCTOCRYLENE 4 g/100 mL; OCTISALATE 5 g/100 mL
INACTIVE INGREDIENTS: ISODODECANE; DIMETHICONE CROSSPOLYMER (450000 MPA.S AT 12% IN CYCLOPENTASILOXANE); DIMETHICONE/BIS-ISOBUTYL PPG-20 CROSSPOLYMER; ISOHEXADECANE; DICAPRYLYL CARBONATE; POLYESTER-7; NEOPENTYL GLYCOL DIHEPTANOATE; POLYMETHYLSILSESQUIOXANE (11 MICRONS); MEDIUM-CHAIN TRIGLYCERIDES; PHYMATOLITHON CALCAREUM; SHEA BUTTER; DIETHYLHEXYL SYRINGYLIDENEMALONATE; MANNITOL; INDIAN FRANKINCENSE; LECITHIN, SUNFLOWER; MICROCRYSTALLINE CELLULOSE; DIATOMACEOUS EARTH; ZINC SULFATE; SILICON DIOXIDE; TOCOPHEROL

Unseen Sunscreen Broad Spectrum SPF 40

Active Ingredients Purpose

Avobenzone 3% Sunscreen

Homosalate 8% Sunscreen

Octocrylene 4% Sunscreen

Octisalate 5% Sunscreen

Uses

- Helps prevent sunburn
- If used as directed with other sun protection measures (see Directions), decreases the risk of skin cancer and early skin aging caused by the sun

Keep out of reach of children. If product is swallowed, get medical help or contact a Poison Control Center right away.

Stop use and ask a doctor if rash occurs

Warnings

For external use only

Do not use on damaged or broken skin

Directions

- apply generously and evenly 15 minutes before sun exposure
- reapply:

after 40 minutes of swimming or sweating

immediately after towel drying

at least every 2 hours

- Sun Protection Measures Spending time in the sun increases your risk of skin cancer and early skin aging. To decrease this risk, regularly use a sunscreen with a Broad Spectrum SPF value of 15 or higher and other sun protection measures including:
- Limit time in the sun, especially from 10 a.m.-2 p.m.
- Wear long-sleeved shirts, pants, hats, and sunglasses
- Children under 6 months: ask a doctor

Inactive Ingredients

Isododecane, Dimethicone Crosspolymer, Dimethicone/Bis-Isobutyl PPG-20 Crosspolymer, Polymethylsilsesquioxane, Isohexadecane, Dicrapylyl Carbonate, Meadowfoam Estolide, Caprylic/Capric Triglyceride, Polyester-7, Neopentyl Glycol Diheptanoate, Lithothamnion Calcareum Extract,Butyrospermum Parkii (Shea) Butter, Jojoba Esters, Mannitol, Boswellia Serrata Resin Extract, Lecithin, Microcrystalline Cellulose, Diatomaceous Earth, Zinc Sulfate, Silica, Tocopherol